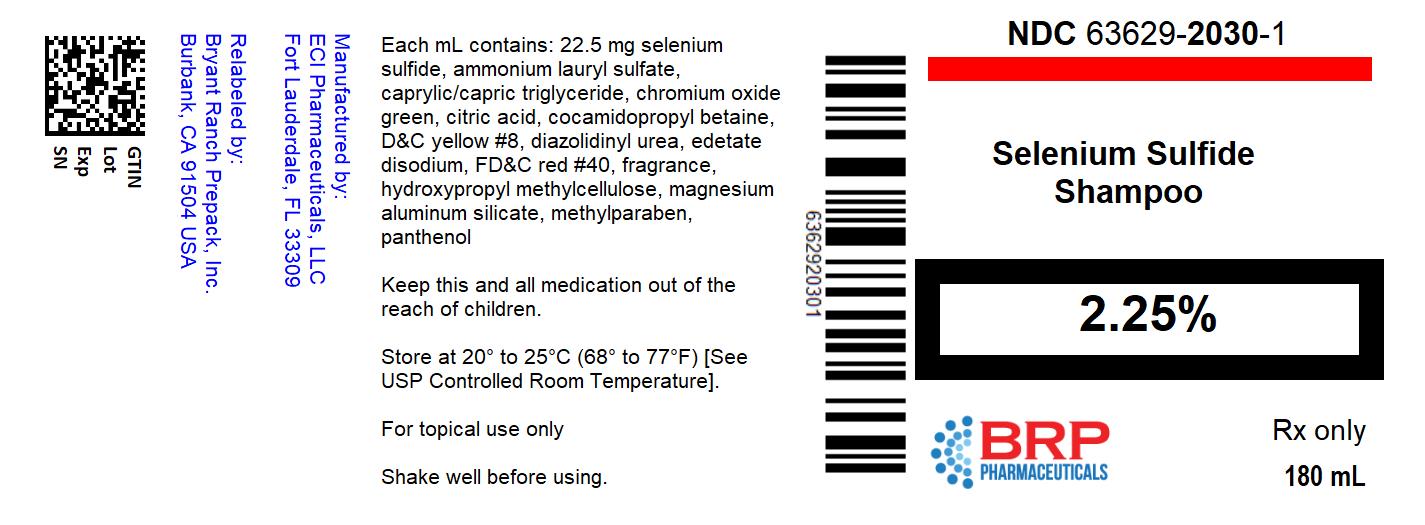 DRUG LABEL: Selenium Sulfide
NDC: 63629-2030 | Form: SHAMPOO
Manufacturer: Bryant Ranch Prepack
Category: prescription | Type: HUMAN PRESCRIPTION DRUG LABEL
Date: 20220415

ACTIVE INGREDIENTS: SELENIUM SULFIDE 22.5 mg/1 mL
INACTIVE INGREDIENTS: AMMONIUM LAURYL SULFATE; TRICAPRIN; CHROMIC OXIDE; CITRIC ACID MONOHYDRATE; COCAMIDOPROPYL BETAINE; FLUORESCEIN SODIUM; DIAZOLIDINYL UREA; EDETATE DISODIUM; FD&C RED NO. 40; HYPROMELLOSE, UNSPECIFIED; MAGNESIUM ALUMINUM SILICATE; METHYLPARABEN; PANTHENOL; PPG-2 HYDROXYETHYL COCO/ISOSTEARAMIDE; PROPYLENE GLYCOL; PROPYLPARABEN; WATER; SODIUM CITRATE, UNSPECIFIED FORM; TITANIUM DIOXIDE; .ALPHA.-TOCOPHEROL ACETATE; UREA; PYRITHIONE ZINC

Selenium Sulfide
2.25% Shampoo

Rx Only

DIRECTIONS

A liquid antiseborrehic, antifungal preparation for topical application.

Each mL of Selenium Sulfide 2.25% Shampoo contains 22.5 mg selenium sulfide, ammonium lauryl sulfate, caprylic/capric triglyceride, chromium oxide green, citric acid, cocamidopropyl betaine, D&C yellow #8, diazolidinyl urea, edetate disodium, FD&C red #40, fragrance, hydroxypropyl methylcellulose, magnesium aluminum silicate, methylparaben, panthenol, PPG-2 hydroxyethyl coco/isostearamide, propylene glycol, propylparaben, purified water, sodium citrate, titanium dioxide, tocopheryl acetate, urea, zinc pyrithione.

CLINICAL PHARMACOLOGY

Selenium sulfide appears to have a cytostatic effect on cells of the epidermis and follicular epithelium, reducing corneocyte production.

PHARMACOKINETICS

The mechanism of action of topically applied selenium sulfide is not yet known.

INDICATIONS & USAGE

A liquid antiseborrheic, antifungal preparation for the treatment of seborrheic dermatitis of the scalp, dandruff and tinea versicolor. Urea hydrates and is useful for conditions such as dry scalp.

CONTRAINDICATIONS

Contraindicated in persons with known or suspected hypersensitivity to any of the listed ingredients.

WARNINGS

For external use only. Not for ophthalmic use. DO NOT USE ON BROKEN SKIN OR INFLAMED AREAS. If allergic reaction occurs, discontinue use. Avoid contact with eyes, genital areas and skin folds, as irritation and burning may result. If accidental contact occurs, rinse thoroughly with water.

PRECAUTIONS

This medication is to be used as directed by a physician. Not to be used when inflammation or exudation is present as increased absorption may occur.

CARCINOGENESIS

Dermal application of 25% and 50% solutions of 2.5% selenium sulfide lotion on mice over an 88-week period indicated no carcinogenic effects.

USE IN PREGNANCY

CATEGORY C

Animal reproduction studies have not been conducted with this medication. It is also not known whether this product can cause fetal harm when applied to the body surfaces of a pregnant woman or can affect reproduction capacity. Under ordinary circumstances, selenium sulfide 2.25% shampoo should not be used by pregnant women.

NURSING MOTHERS

It is not known whether or not this drug is secreted in human milk. Because many drugs are secreted in human milk, caution should be exercised when this product is administered to a nursing woman.

PEDIATRIC USE

Safety and effectiveness in children have not been established.

ADVERSE REACTIONS

In decreasing order of severity: skin irritation; occasional reports of increase in normal hair loss; discoloration of hair (can be avoided or minimized by thorough rinsing of hair after treatment). As with other shampoos, oiliness or dryness of hair and scalp may occur.

OVERDOSAGE

There are no documented reports of serious toxicity in humans resulting from acute ingestion of selenium sulfide 2.25% shampoo. However, acute toxicity studies in animals suggest that ingestion of large amounts could result in potential human toxicity. Evacuation of the stomach contents should be considered in cases of acute oral ingestion.

DOSAGE AND ADMINISTRATION

SHAKE WELL BEFORE USING

For seborrheic dermatitis and dandruff

Generally 2 applications each week for 2 weeks will control symptoms. Subsequently, shampoo may be used less frequently – weekly, every 2 weeks, every 3 to 4 weeks or as directed by a physician. Should not be applied more frequently than necessary to maintain control.

For tinea versicolor

Apply to affected areas and lather with a small amount of water. Allow product to remain on skin for 10 minutes, then rinse thoroughly. Repeat procedure once a day for seven days or as directed by a physician.

HOW SUPPLIED

Selenium Sulfide 2.25% Shampoo is supplied in 180 mL bottles, NDC 63629-2030-1.

Store at 20°C to 25°C (68°F to 77°F), excursions permitted between 15°C and 30°C (between 59°F and 86°F). Brief exposure to temperatures up to 40°C (104°F) may be tolerated provided the mean kinetic temperature does not exceed 25°C (77°F); however, such exposure should be minimized. Protect from freezing.

KEEP THIS AND ALL MEDICATIONS OUT OF THE REACH OF CHILDREN.

Manufactured for:
Noble Pharmaceuticals LLC
Cooper City, FL 33024

1/17

PACKAGE LABEL

Selenium Sulfide 22.5 mg Shampoo, #180mL